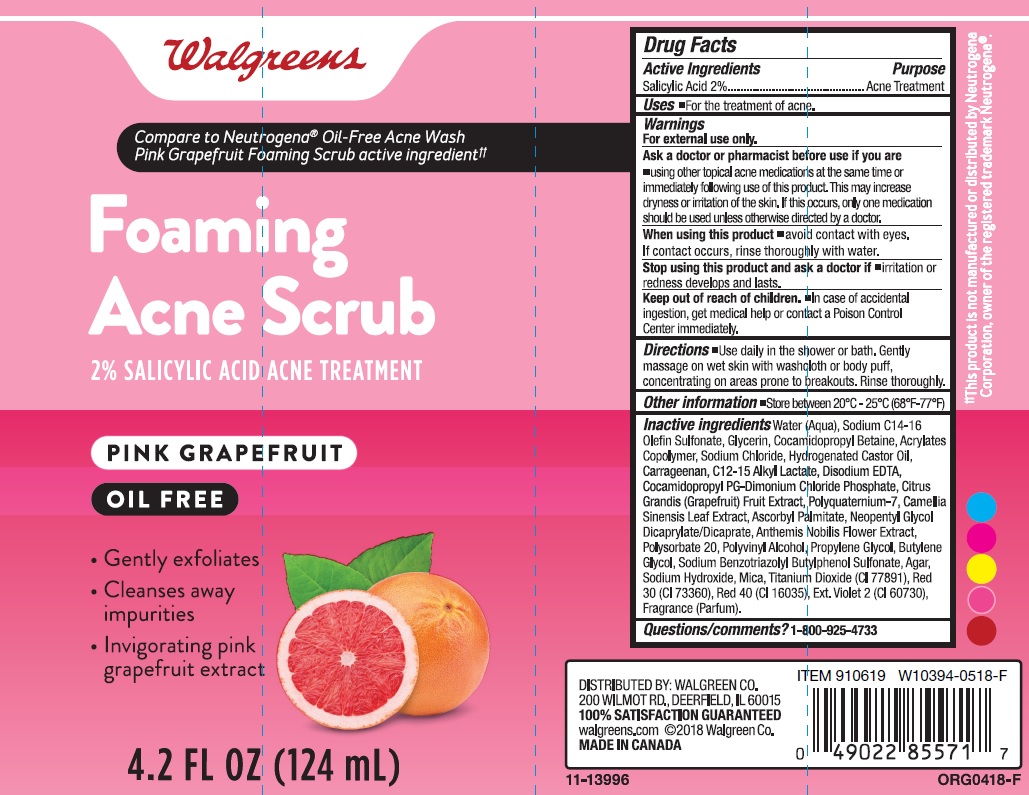 DRUG LABEL: Walgreens Foaming Acne Scrub
NDC: 0363-8290 | Form: LIQUID
Manufacturer: Walgreen Company
Category: otc | Type: HUMAN OTC DRUG LABEL
Date: 20180620

ACTIVE INGREDIENTS: SALICYLIC ACID 20 mg/1 mL
INACTIVE INGREDIENTS: WATER; SODIUM C14-16 OLEFIN SULFONATE; GLYCERIN; COCAMIDOPROPYL BETAINE; CARBOMER COPOLYMER TYPE A (ALLYL PENTAERYTHRITOL CROSSLINKED); SODIUM CHLORIDE; HYDROGENATED CASTOR OIL; CARRAGEENAN; C12-15 ALKYL LACTATE; EDETATE SODIUM; COCAMIDOPROPYL PG-DIMONIUM CHLORIDE PHOSPHATE; PUMMELO; POLYQUATERNIUM-7 (70/30 ACRYLAMIDE/DADMAC; 1600000 MW); GREEN TEA LEAF; ASCORBYL PALMITATE; NEOPENTYL GLYCOL DICAPRYLATE/DICAPRATE; CHAMAEMELUM NOBILE FLOWER; POLYSORBATE 20; POLYVINYL ALCOHOL (100000 MW); PROPYLENE GLYCOL; BUTYLENE GLYCOL; SODIUM BENZOTRIAZOLYL BUTYLPHENOL SULFONATE; AGAR; SODIUM HYDROXIDE; MICA; TITANIUM DIOXIDE; D&C RED NO. 33; FD&C RED NO. 40; EXT. D&C VIOLET NO. 2

Drug Facts

Active ingredient

Salicylic Acid 2%

Purpose

Acne Treatment

Uses

- For the treatment of acne.

Warnings

For external use only.

Ask a doctor of pharmacist before use if you are

- using other topical acne medications at the same time or immediately following use of this product. This may increase dryness or irritation of the skin. If this occurs, only one medication should be used unless otherwise directed by a doctor.

When using this product

- avoid contact with eyes. If contact occurs, rinse thoroughly with water.

Stop using this product and ask a doctor if

- irritation or redness develops and lasts.

Keep out of reach of children.

- In case of accidental ingestion, get medical help or contact a Poison Control Center immediately.

Directions

- Use daily in the shower or bath. Gently massage on wet skin with washcloth or body puff, concentrating on areas prone to breakouts. Rinse thoroughly.

Other information

- store between 20°C - 25°C (68°F - 77°F)

Inactive ingredients

Water (Aqua), Sodium C14-16 Olefin Sulfonate, Glycerin, Cocamidopropyl Betaine, Acrylates Copolymer, Sodium Chloride, Hydrogenated Castor Oil, Carrageenan, C12-15 Alkyl Lactate, Disodium EDTA, Cocamidopropyl PG-Dimonium Chloride Phosphate, Citrus Grandis (Grapefruit) Fruit Extract, Polyquaternium-7, Camellia Sinensis Leaf Extract, Ascorbyl Palmitate, Neopentyl Glycol Dicaprylate/Dicaprate, Anthemis Nobilis Flower Extract, Polysorbate 20, Polyvinyl Alcohol, Propylene Glycol, Butylene Glycol, Sodium Benzotriazolyl Butylphenol Sulfonate, Agar, Sodium Hydroxide, Mica, Titanium Dioxide (CI 77891), Red 30 (CI 73360), Red 40 (CI 16035), Ext. Violet 2 (CI 60730), Fragrance (Parfum).

Questions/comments?

1-800-925-4733